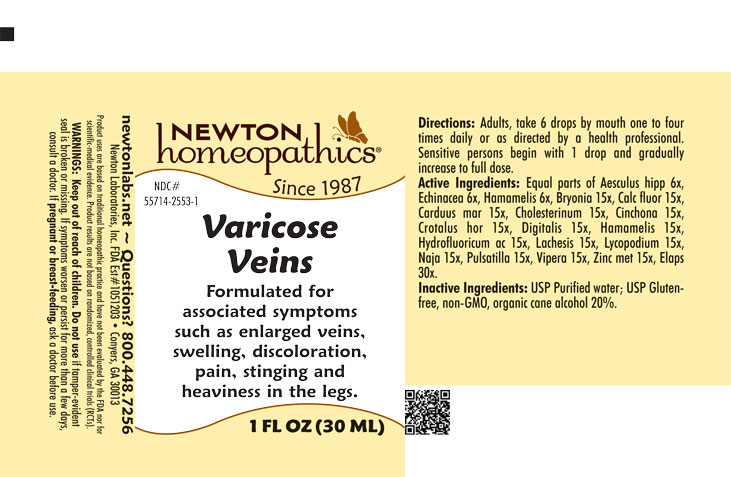 DRUG LABEL: Varicose Veins
NDC: 55714-2553 | Form: LIQUID
Manufacturer: Newton Laboratories, Inc.
Category: homeopathic | Type: HUMAN OTC DRUG LABEL
Date: 20260129

ACTIVE INGREDIENTS: MICRURUS CORALLINUS VENOM 30 [hp_X]/1 mL; CROTALUS HORRIDUS HORRIDUS VENOM 15 [hp_X]/1 mL; BRYONIA ALBA ROOT 15 [hp_X]/1 mL; CALCIUM FLUORIDE 15 [hp_X]/1 mL; SILYBUM MARIANUM SEED 15 [hp_X]/1 mL; CHOLESTEROL 15 [hp_X]/1 mL; CINCHONA OFFICINALIS BARK 15 [hp_X]/1 mL; DIGITALIS 15 [hp_X]/1 mL; HAMAMELIS VIRGINIANA ROOT BARK/STEM BARK 15 [hp_X]/1 mL; HYDROFLUORIC ACID 15 [hp_X]/1 mL; LACHESIS MUTA VENOM 15 [hp_X]/1 mL; LYCOPODIUM CLAVATUM SPORE 15 [hp_X]/1 mL; NAJA NAJA VENOM 15 [hp_X]/1 mL; PULSATILLA VULGARIS 15 [hp_X]/1 mL; VIPERA BERUS VENOM 15 [hp_X]/1 mL; ZINC 15 [hp_X]/1 mL; HORSE CHESTNUT 6 [hp_X]/1 mL; ECHINACEA, UNSPECIFIED 6 [hp_X]/1 mL
INACTIVE INGREDIENTS: ALCOHOL; WATER

Varicose 2553L

INDICATIONS & USAGE SECTION

Formulated for associated symptoms such as enlarged veins, swelling, discoloration, pain, stinging and heaviness in the legs.

DOSAGE & ADMINISTRATION SECTION

Directions: Adults, take 6 drops by mouth one to four times daily or as directed by a health professional. Sensitive persons begin with 1 drop and gradually increase to full dose.

OTC - ACTIVE INGREDIENT SECTION

Equal parts of Aesculus hipp. 6x, Echinacea 6x, Hamamelis 6x, Bryonia 15x, Calc. fluor. 15x, Carduus mar. 15x, Cholesterinum 15x, Cinchona 15x, Crotalus hor. 15x, Digitalis 15x, Hamamelis 15x, Hydrofluoricum acidum 15x, Lachesis 10x, Lycopodium 15x, Naja 15x, Pulsatilla 15x, Vipera berus 15x, Zinc. met. 15x, Elaps 30x.

OTC - PURPOSE SECTION

Formulated for associated symptoms such as enlarged veins, swelling, discoloration, pain, stinging and heaviness in the legs.

INACTIVE INGREDIENT SECTION

Inactive Ingredients: USP Purified Water; USP Gluten-free, non-GMO, organic cane alcohol 20%.

QUESTIONS SECTION

newtonlabs.net - Questions? 800.448.7256

Newton Laboratories, Inc. FDA Est # 1051203 - Conyers, GA 30013

OTC - PREGNANCY OR BREAST FEEDING SECTION

If pregnant or breast-feeding, ask a doctor before use.

OTC - KEEP OUT OF REACH OF CHILDREN SECTION

Keep out of reach of children.